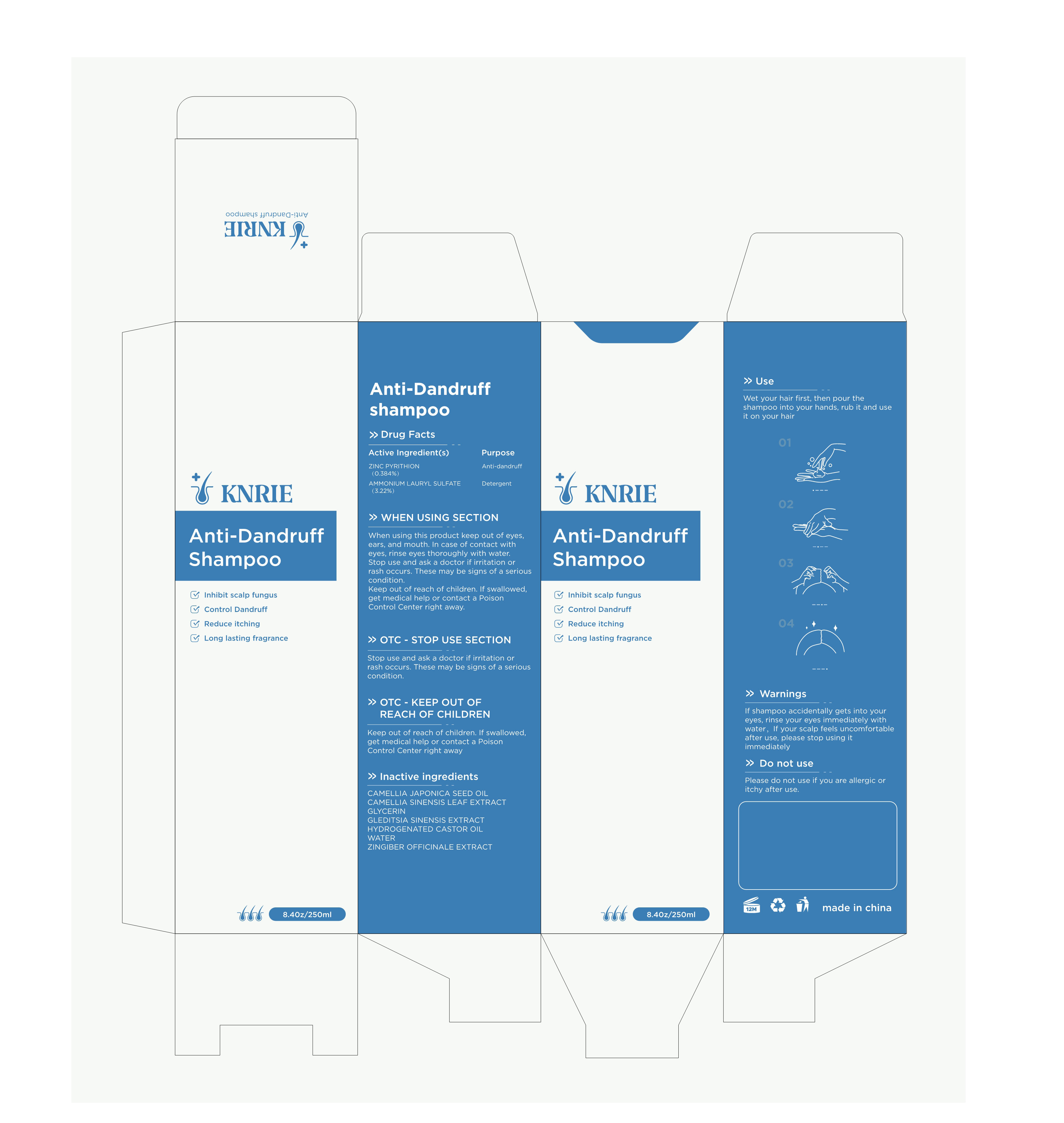 DRUG LABEL: Anti-Dandruff
NDC: 83619-002 | Form: SHAMPOO
Manufacturer: Shenzhen Derbit Technology Co., Ltd.
Category: otc | Type: HUMAN OTC DRUG LABEL
Date: 20240110

ACTIVE INGREDIENTS: PYRITHIONE ZINC 0.384 g/100 mL; AMMONIUM LAURYL SULFATE 3.22 g/100 mL
INACTIVE INGREDIENTS: CAMELLIA JAPONICA SEED OIL; WATER; GLYCERIN; GREEN TEA LEAF; HYDROGENATED CASTOR OIL; GINGER; GLEDITSIA SINENSIS WHOLE

Active ingredient

ZINC PYRITHION (0.384%)

AMMONIUM LAURYL SULFATE (3.22%)

purpose

Anti-dandruff

Detergent

use

Wet your hair first, then pour the shampoo into your hands, rub it and use it on your hair

Warning

If shampoo accidentally gets into your eyes, rinse your eyes immediately with water，If your scalp feels uncomfortable after use, please stop using it immediately

Do not use

Please do not use if you are allergic or itchy after use.

When using SECTION

When using this product keep out of eyes, ears, and mouth. In case of contact with eyes, rinse eyes thoroughly with water.
Stop use and ask a doctor if irritation or rash occurs. These may be signs of a serious condition.
Keep out of reach of children. If swallowed, get medical help or contact a Poison Control Center right away.

OTC-STOP USE SECTION

Stop use and ask a doctor if irritation or rash occurs. These may be signs of a serious condition.

Keep out of reach of children. If swallowed, get medical help or contact a Poison Control Center right away.

Direction

n/a

STORAGE AND HANDLING

n/a

inactive ingredients

CAMELLIA JAPONICA SEED OIL

CAMELLIA SINENSIS LEAF EXTRACT

GLYCERIN

GLEDITSIA SINENSIS EXTRACT

HYDROGENATED CASTOR OIL

WATER

ZINGIBER OFFICINALE EXTRACT